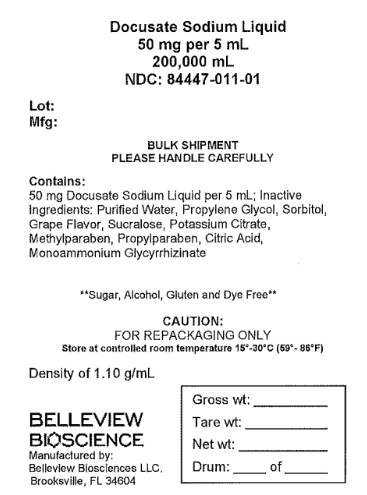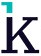 DRUG LABEL: Docusate Sodium
NDC: 84447-011 | Form: LIQUID
Manufacturer: Belleview Bio Science
Category: otc | Type: HUMAN OTC DRUG LABEL
Date: 20250422

ACTIVE INGREDIENTS: DOCUSATE SODIUM 100 mg/10 mL
INACTIVE INGREDIENTS: PROPYLPARABEN; CITRIC ACID MONOHYDRATE; PROPYLENE GLYCOL; POTASSIUM CITRATE; SUCRALOSE; GRAPE; SORBITOL; AMMONIUM GLYCYRRHIZATE; WATER; METHYLPARABEN

Docusate Sodium Oral Liquid

Active Ingredient (in each 10 mL)

Docusate Sodium 100 mg

Purpose

Stool Softener Laxative

Uses

- relieves of occasional constipation (irregularity)
- generally produces bowel movement in 12 to 72 hours

Warnings

Do not use

- for more than 1 week unless directed by a doctor
- if you are currently taking mineral oil, unless directed by a doctor

Ask a doctor before use if you have

- stomach pain
- nausea
- vomiting
- noticed a sudden change in bowel habits that persist over a period of 2 weeks

Stop use and ask a doctor if

- you have rectal bleeding or failure to have a bowel movement after use of a laxative. These could be signs of a serious condition.
- a skin rash occurs
- you experience throat irritation

If pregnant or breast-feeding,

ask a health professional before use.

OVERDOSAGE

In case of overdosage, get medical help or contact a Poison Control Center right away.

Directions

- shake well before using
- must be given in a 6 oz to 8 oz glass of milk, fruit juice or infant formula to mask the bitter taste and prevent throat irritation
- take maximum dose daily until first bowel movement, dosage should then be reduced according to individual response
- do not exceed recommended dose
- follow dosing directions below or use as directed by a doctor

1 teaspoonful = 5 mL
Age | Dose
adults and children 12 years and older | 1 to 7 teaspoonfuls
children 2 to under 12 years of age | 1 to 3 teaspoonfuls
children under 2 years of age | ask a doctor

Other Information

- store at controlled room temperature 20ºC to 25ºC (68ºF to 77ºF)
- protect from light
- protect from excessive heat
- protect from freezing
- clear, grape-flavored liquid, supplied in the following:

NDC 81033-022-10: 10 mL unit dose cup

NDC 81033-022-50: Case containing 100 unit dose cups of 10 mL each

Inactive ingredients

citric acid, grape flavor, methylparaben, monoammonium glycyrrhizinate, potassium citrate, propylene glycol, propylparaben, purified water, sorbitol, sucralose

Questions or comments?

Call 1-833-537-4679

Packaged by:

Kesin Pharma

Oldsmar, FL 34677

Rev. 04/2025

PACKAGE LABEL

BULK SHIPMENT: For institutional or repackaging use only.

Docusate Sodium Liquid

50 mg per 5 mL

200,00 mL

NDC: 8447-011-01